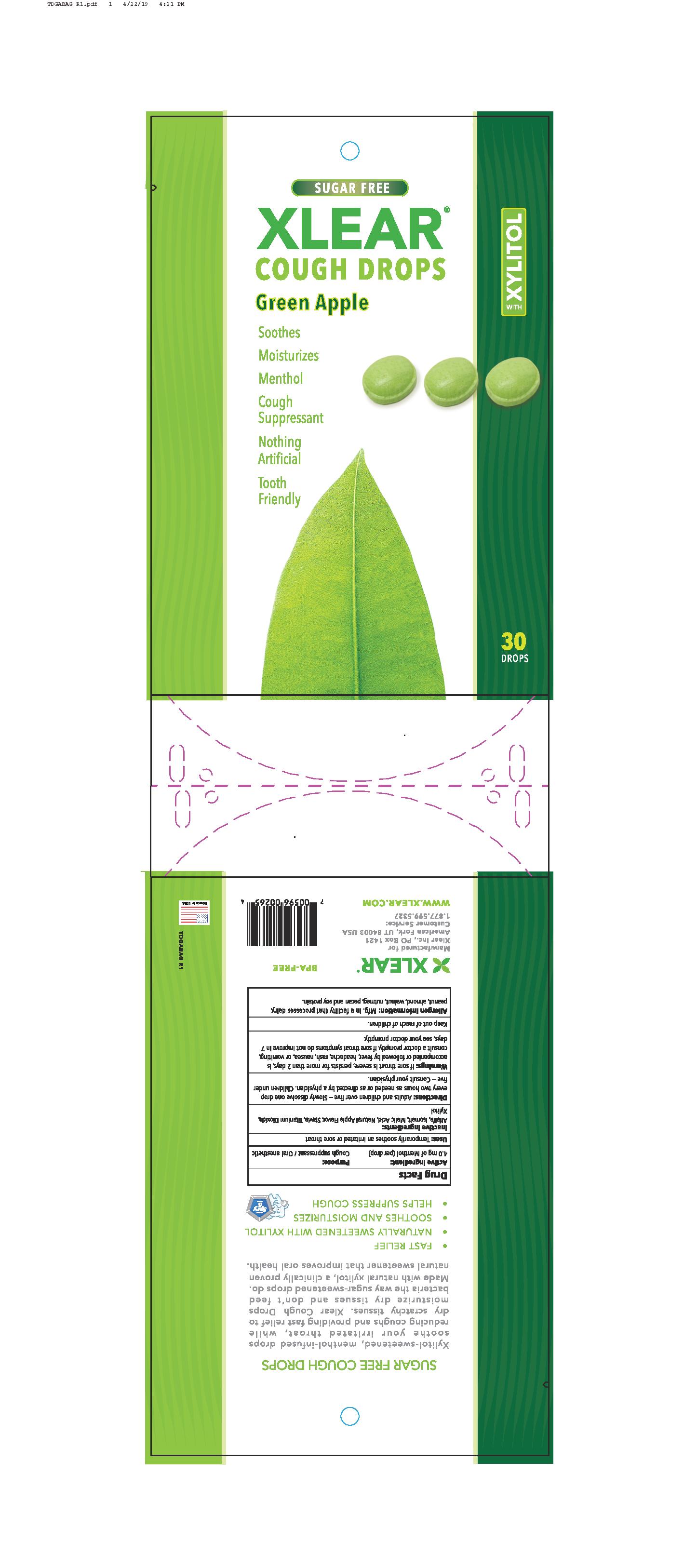 DRUG LABEL: Xlear Cough Drops (Green Apple)
NDC: 27017-021 | Form: LOZENGE
Manufacturer: Xlear Inc.
Category: otc | Type: HUMAN OTC DRUG LABEL
Date: 20230110

ACTIVE INGREDIENTS: MENTHOL 4 mg/1 1
INACTIVE INGREDIENTS: XYLITOL; MALIC ACID; STEVIA LEAF; ISOMALT; TITANIUM DIOXIDE; ALFALFA

Xlear Cough Drops (Green Apple)

ACTIVE INGREDIENT

4.0mg of Menthol (per drop)

PURPOSE

Cough Suppressant / Oral Anesthetic

INDICATIONS AND USAGE

Temporarily soothes an irritated or sore throat

INACTIVE INGREDIENT

Alfalfa, Isomalt, Malic Acid, Natural Apple Flavor, Stevia, Titanium Dioxide, Xytitol

DOSAGE AND ADMINISTRATION

Adults and children over five - Slowly dissolve one drop every two hours as needed or as directed by a physician. Children under five - Consult your physician.

WARNINGS

If sore throat is severe, persists for more than 2 days, is accompanied or followed by fever, headache, rash, nausea, or vomiting, consult a doctor promptly. If sore throat symptoms do not improve in 7 days, see your doctor promptly.

Keep out of reach of children.

OTHER SAFETY INFORMATION

Mfg. in a facility that processes dairy, peanut, almond, walnut, nutmeg, pecan, and soy protein.